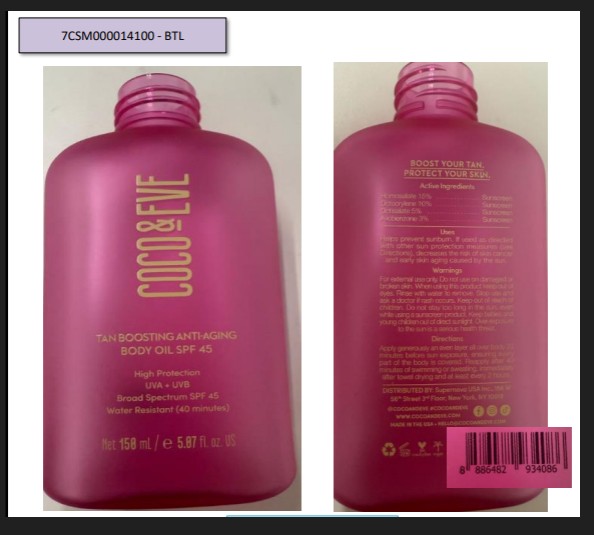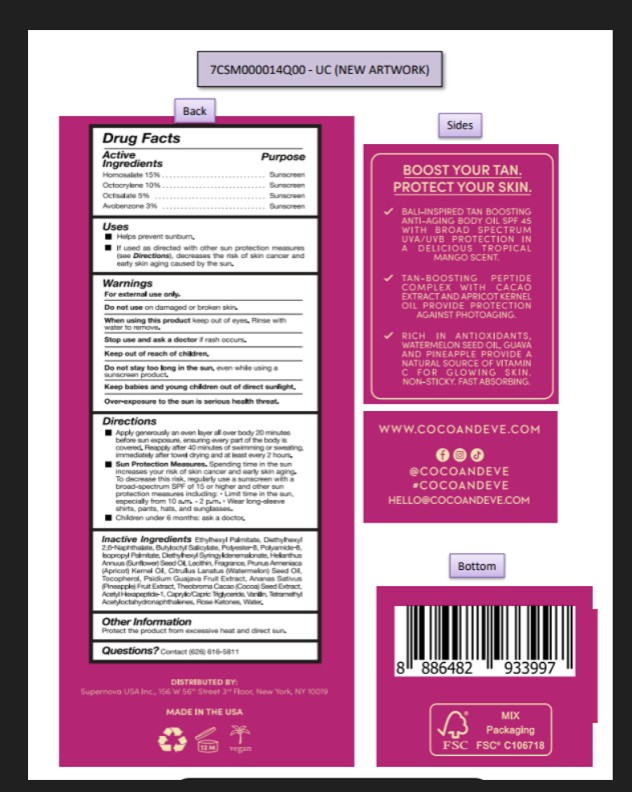 DRUG LABEL: Coco and Eve Tan Boosting Anti Aging Body Oil SPF 45
NDC: 68577-222 | Form: OIL
Manufacturer: COSMAX USA, CORP
Category: otc | Type: HUMAN OTC DRUG LABEL
Date: 20251223

ACTIVE INGREDIENTS: HOMOSALATE 15 mg/100 mL; OCTOCRYLENE 10 mg/100 mL; OCTISALATE 5 mg/100 mL; AVOBENZONE 3 mg/100 mL
INACTIVE INGREDIENTS: THEOBROMA CACAO (COCOA) SEED POWDER; BUTYLOCTYL SALICYLATE; POLYAMIDE-8 (4500 MW); CAPRYLIC/CAPRIC TRIGLYCERIDE; PENTAERYTHRITYL TETRA-DI-T-BUTYL HYDROXYHYDROCINNAMATE; DIETHYLHEXYL SYRINGYLIDENEMALONATE; APRICOT KERNEL OIL; ISOPROPYL PALMITATE; WATER; PSIDIUM GUAJAVA FRUIT; HELIANTHUS ANNUUS (SUNFLOWER) SEED OIL; ETHYLHEXYL PALMITATE; DIETHYLHEXYL 2,6-NAPHTHALATE; POLYESTER-8 (1400 MW, CYANODIPHENYLPROPENOYL CAPPED); LECITHIN, SUNFLOWER; TOCOPHEROL; ANANAS SATIVUS (PINEAPPLE) FRUIT; ACETYL HEXAPEPTIDE-1; CITRULLUS LANATUS (WATERMELON) SEED OIL

COCO & EVE Tan Boosting Anti-Aging Body Oil SPF45

Active Ingredients

Homosalate 15%

Octocrylene 10%

Octisalate 5%

Avobenzone 3%

Purpose

Sunscreen

USES

- Helps prevent sunburn
- If used as directed with other sun protection measures (see Directions), decreases the risk of skin cancer and early skin aging caused by the sun.

Warnings

For external use only.

Do not use on damaged or broken skin.

When using this product keep out of eyes. rinse with water to remove.

Stop use and ask a doctor if rash occurs.

Keep out of reach of children.

DO NOT USE

Do not stay too long in the sun, even while using a sunscreen product.

Keep babies and young children out of direct sunlight.

Over-exposure to the sun i serious health threat

DIRECTIONS

- Appply generously an even layer all over body 20 minutes before sun exposure, ensuring every part of the body is covered. Reapply after 40 minutes of swimming or sweating, immediately after towel drying and at least every 2 hours.
- Sun Protection Measures. Spending time in the sun increases your risk of skin cancer and early skin aging. To decrease this risk, regularly use a sunscreen with broad-spectrum SPF of 15 or higher and other sun protection measures including.
- Limit time in the sun especially from 10 a.m.-2p.m.
- Wear long-sleeve shirts, pants, hats, and sunglasses.
- Children under 6 months:ask a doctor.

Inactive Ingredients

Ethylhexyl Palmitate, Diethylhexyl 2,6-Naphthalate, Butyloctyl Salicylate, Polyester-8, Polyamide-8, Isopropyl Palmitate, Diethylhexyl Syringylidenemalonate, Helianthus Annuus (Sunflower) Seed Oil, Lecithin, Fragrance, Prunus Armeniaca (Apricot) Kernel Oil, Citrullus Lanatus (Watermelon) Seed Oil, Tocopherol, Psidium Guajava Fruit Extract, Ananas Sativus (Pineapple) Fruit Extract, Theobroma Cacao (Cocoa) Seed Extract, Acetyl Hexapeptide-1, Caprylic/Capric Triglyceride, Vanillin, Tetramethyl Acetyloctahydronaphthalenes, Rose Ketones, Water.

OTHER INFORMATION

Protect the product from excessive heat and direct sun.

Questions?

Contact (626) 616-5811